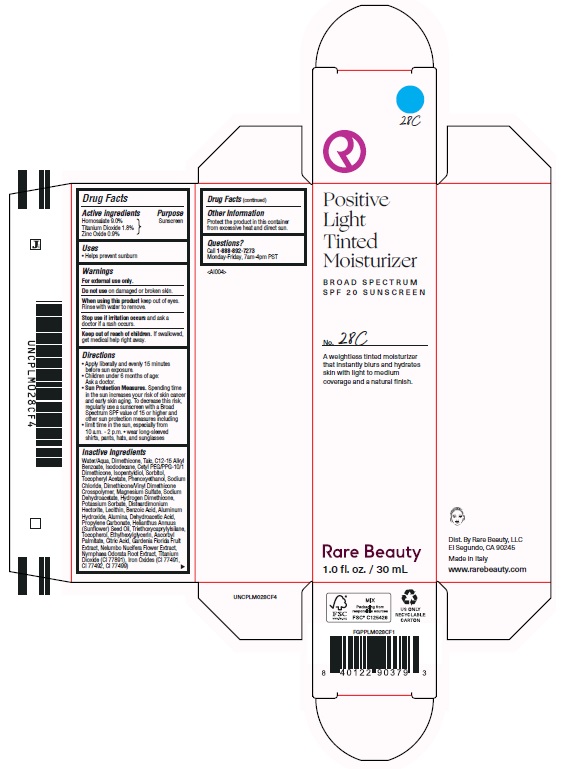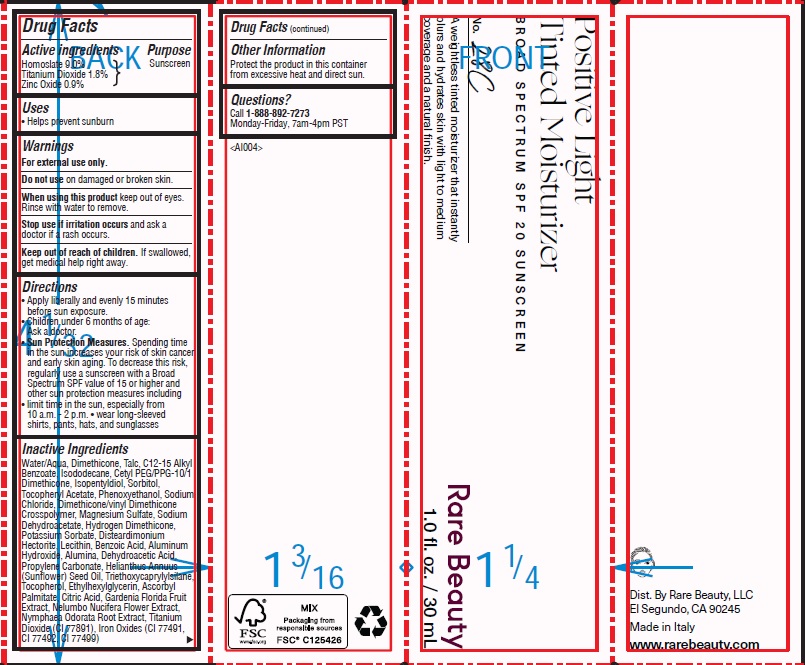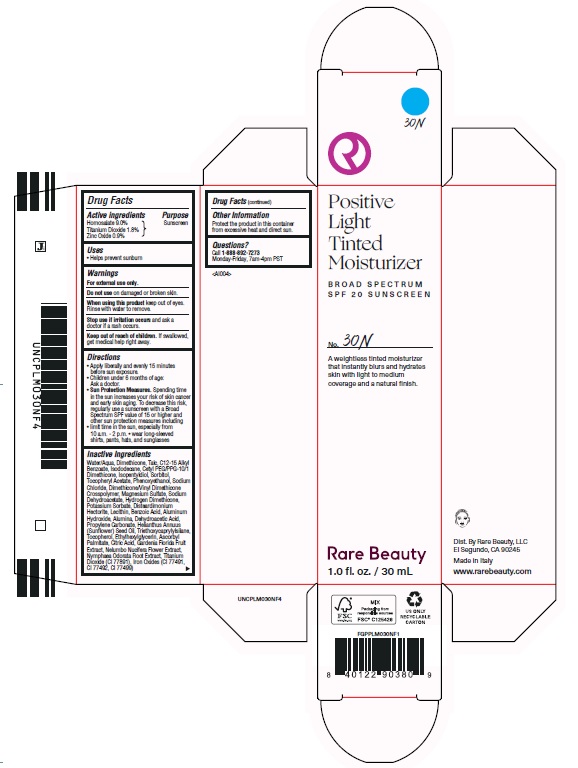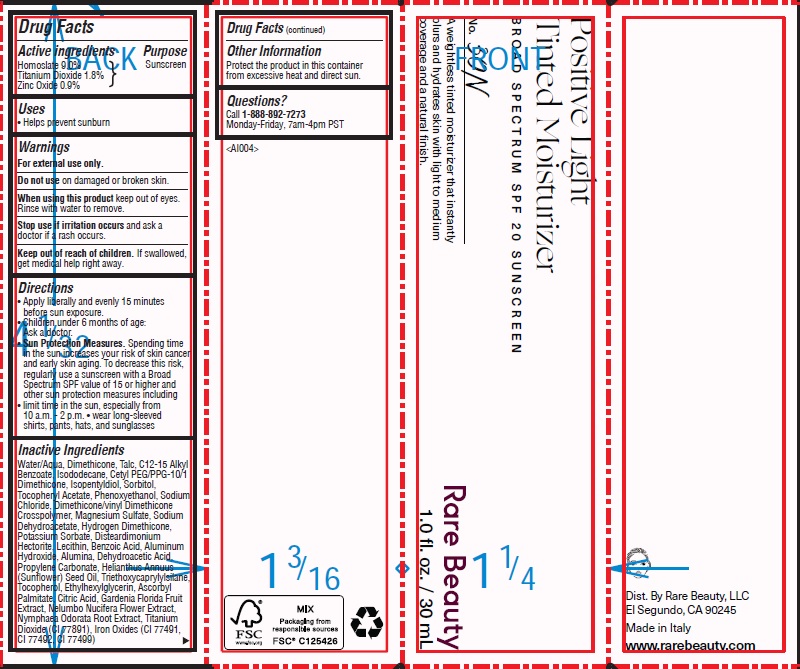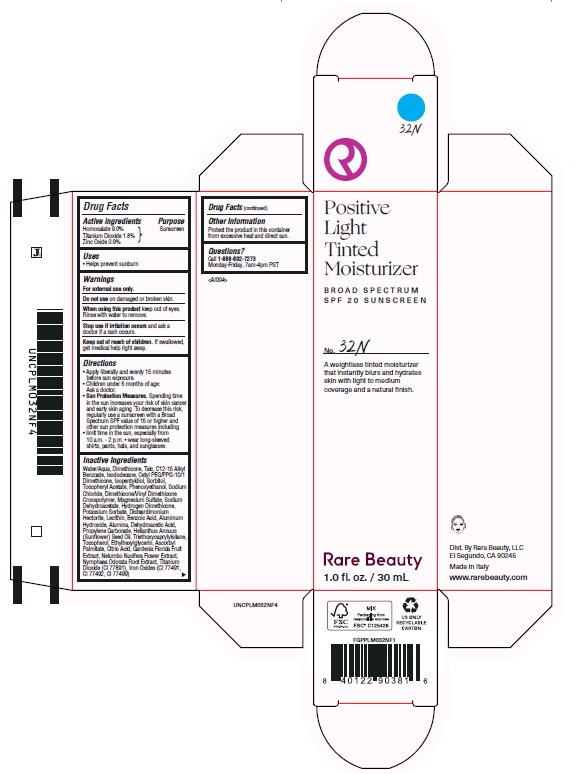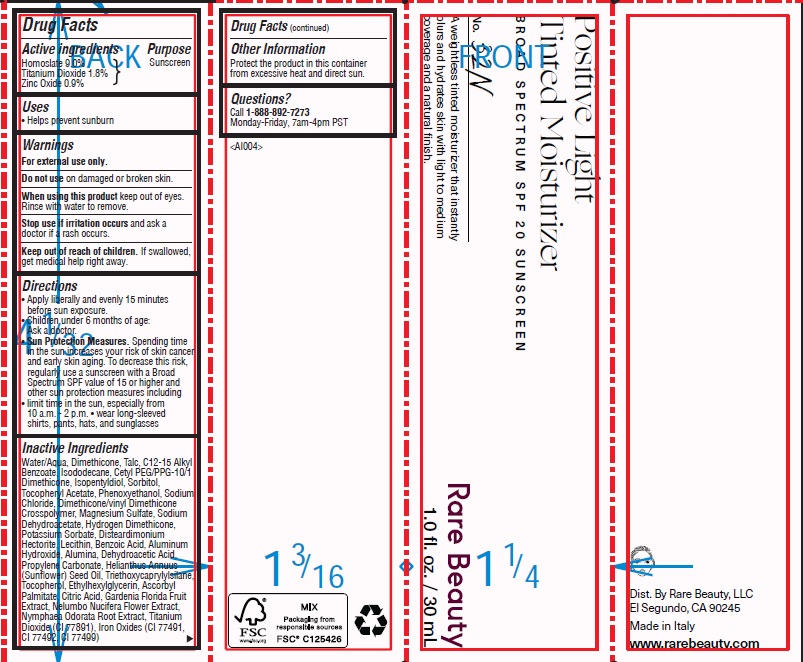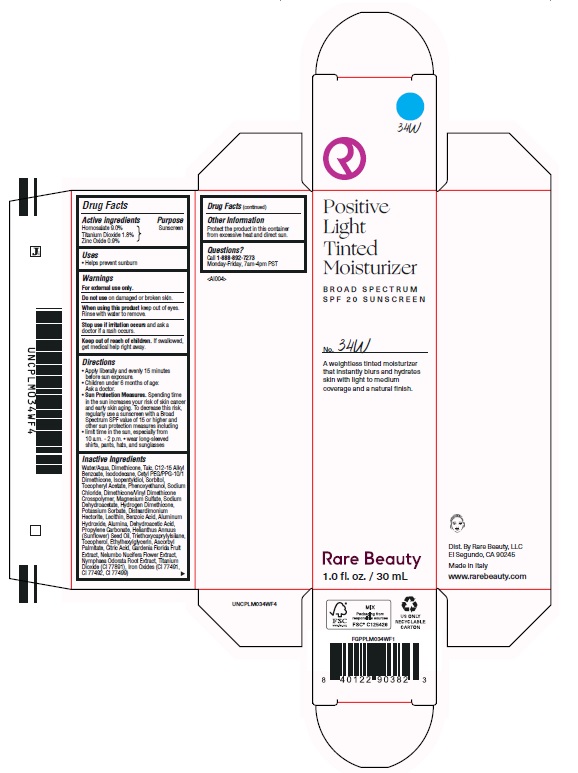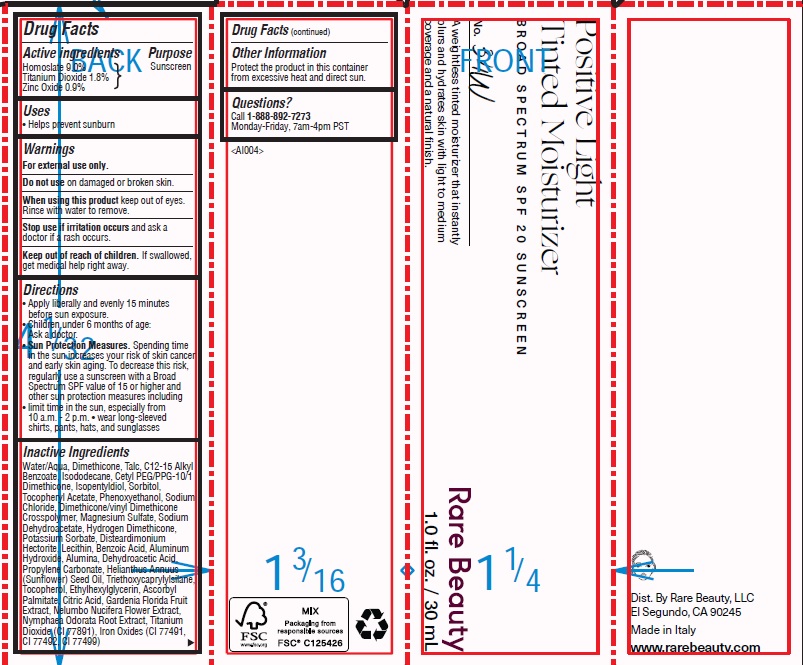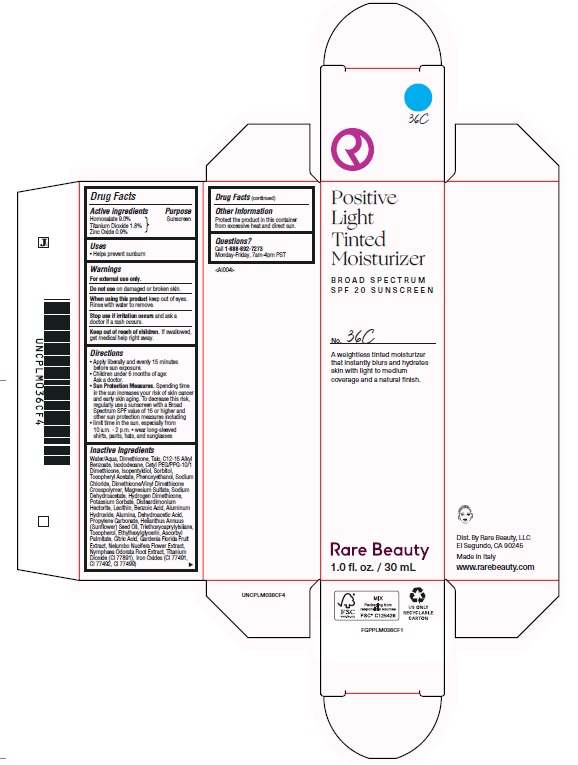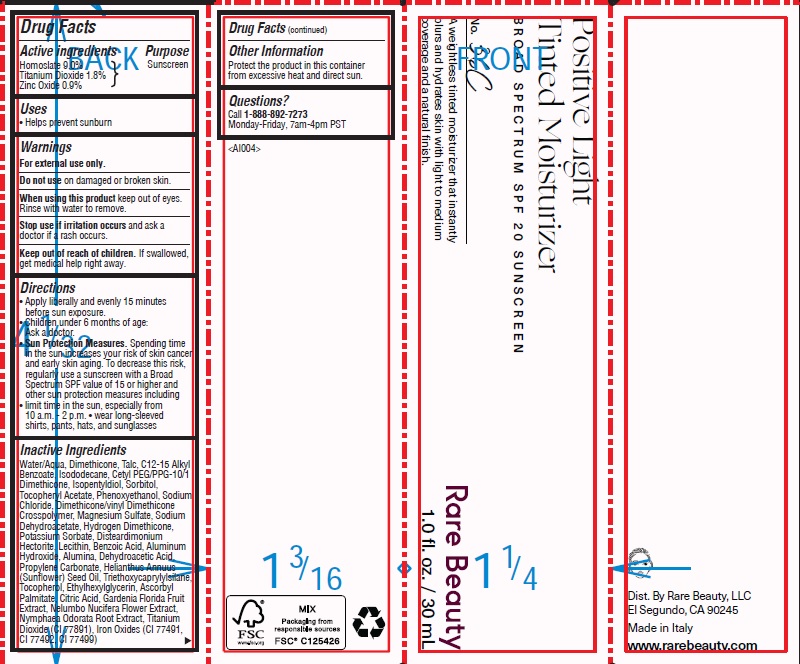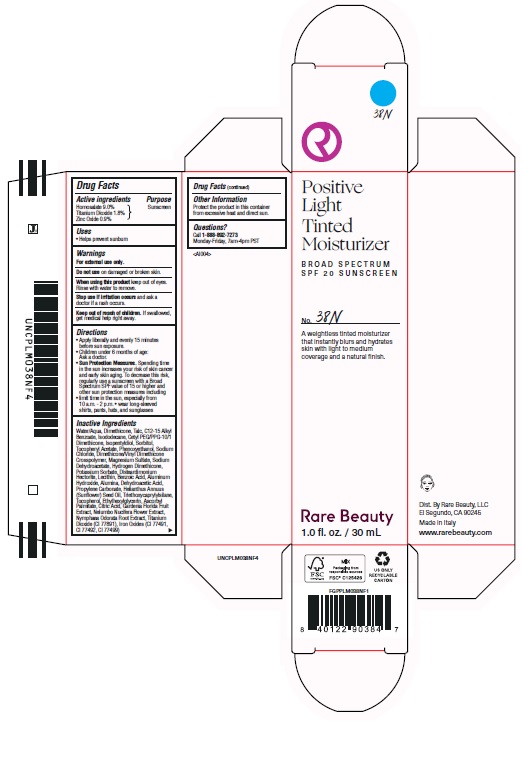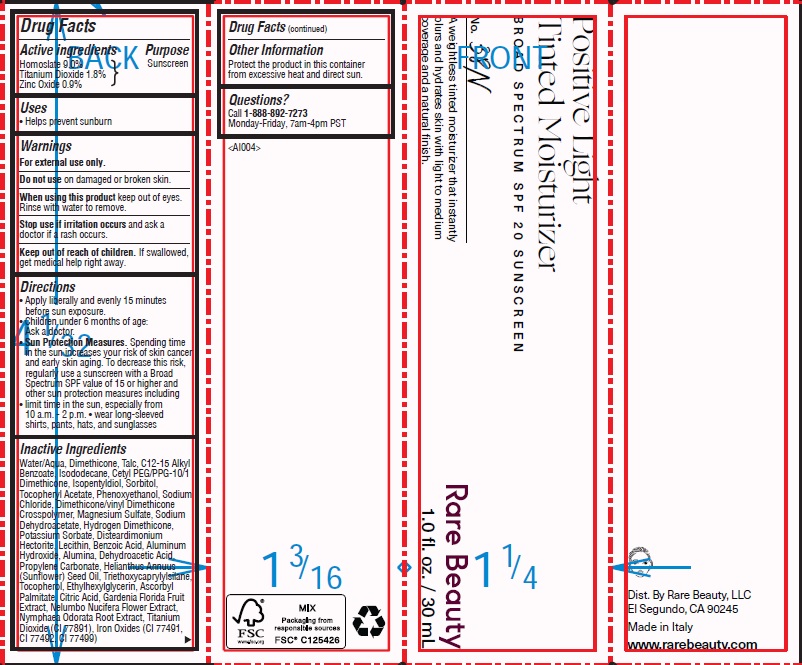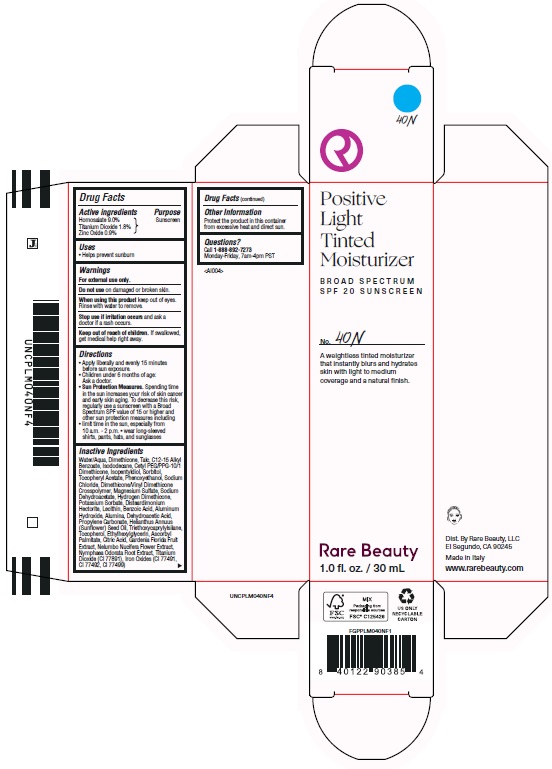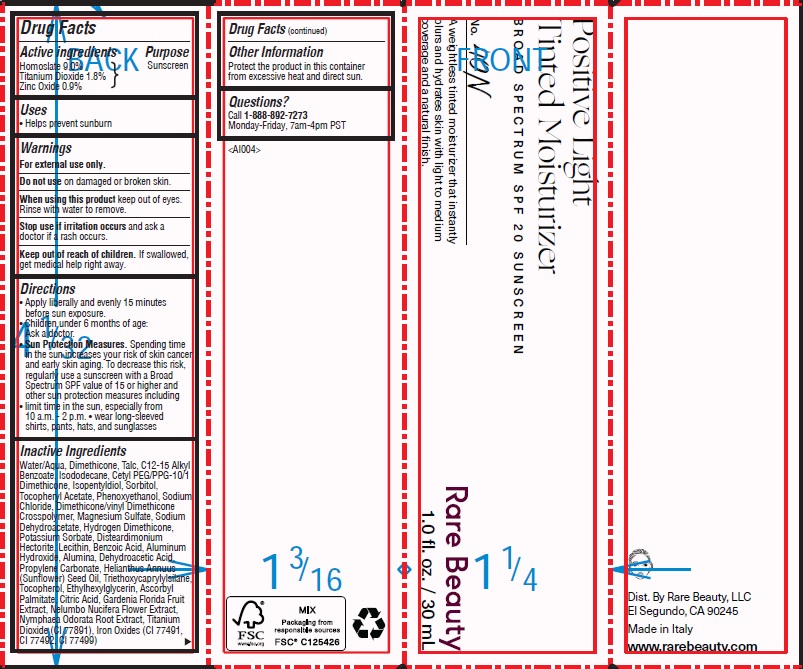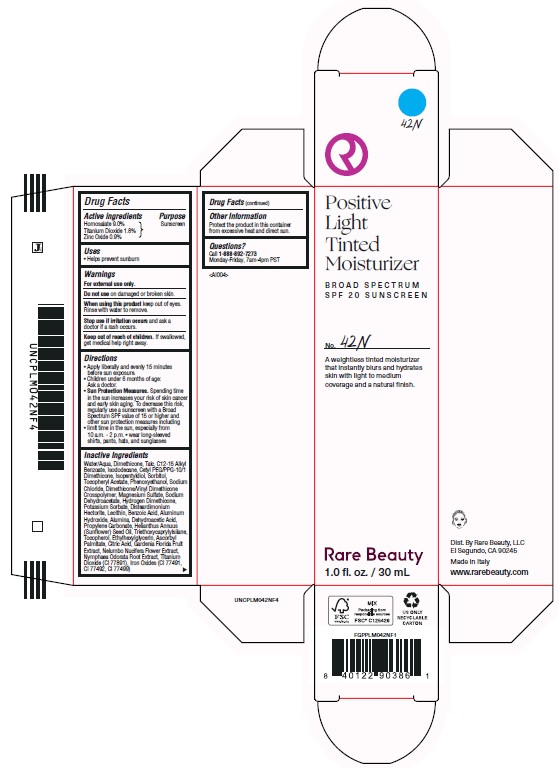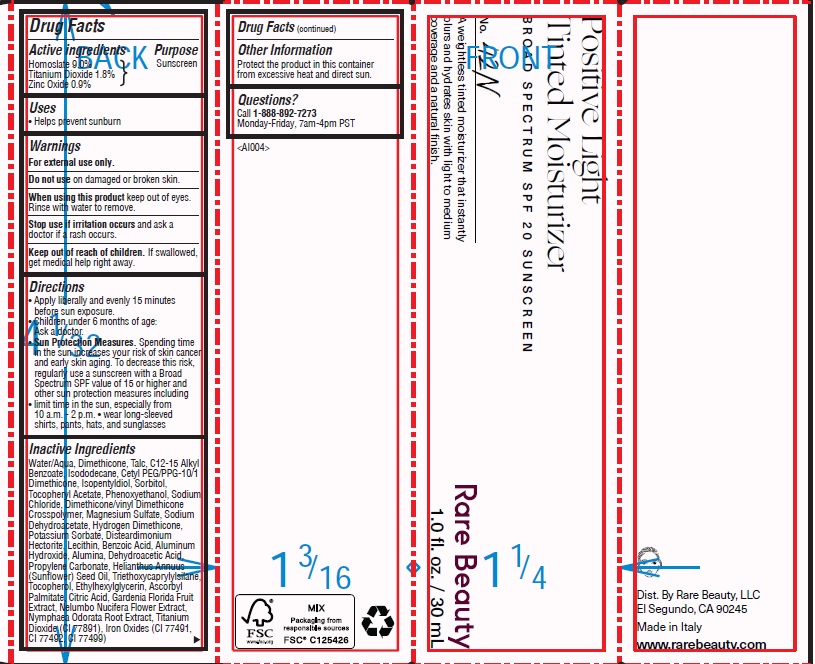 DRUG LABEL: Positive Light Tinted Moisturizer Broad Spectrum SPF 20 Sunscreen 28C
NDC: 82109-108 | Form: LOTION
Manufacturer: Rare Beauty, LLC
Category: otc | Type: HUMAN OTC DRUG LABEL
Date: 20241023

ACTIVE INGREDIENTS: TITANIUM DIOXIDE 18 mg/1 mL; HOMOSALATE 90 mg/1 mL; ZINC OXIDE 9 mg/1 mL
INACTIVE INGREDIENTS: CETYL PEG/PPG-10/1 DIMETHICONE (HLB 5); LECITHIN, SOYBEAN; TRIETHOXYCAPRYLYLSILANE; ALKYL (C12-15) BENZOATE; .ALPHA.-TOCOPHEROL ACETATE; DIMETHICONE/VINYL DIMETHICONE CROSSPOLYMER (SOFT PARTICLE); MAGNESIUM SULFATE, UNSPECIFIED; SODIUM DEHYDROACETATE; SUNFLOWER OIL; NELUMBO NUCIFERA FLOWER; FERRIC OXIDE RED; DIMETHICONE; DISTEARDIMONIUM HECTORITE; ALUMINUM HYDROXIDE; ALUMINUM OXIDE; PROPYLENE CARBONATE; SORBITOL; ISOPENTYLDIOL; PHENOXYETHANOL; SODIUM CHLORIDE; HYDROGEN DIMETHICONE (20 CST); POTASSIUM SORBATE; BENZOIC ACID; WATER; DEHYDROACETIC ACID; TOCOPHEROL; ETHYLHEXYLGLYCERIN; ASCORBYL PALMITATE; CITRIC ACID MONOHYDRATE; NYMPHAEA ODORATA ROOT; FERRIC OXIDE YELLOW; FERROSOFERRIC OXIDE; TALC; ISODODECANE; GARDENIA JASMINOIDES FRUIT

Positive Light Tinted Moisturizer Broad Spectrum SPF 20 Sunscreen

Active ingredients

Homosalate 9.0%

Titanium Dioxide 1.8%

Zinc Oxide 0.9%

Purpose

Sunscreen

Uses

- Helps prevent sunburn

Warnings

For external use only.

Do not use

on damaged or broken skin.

When using this product

keep out of eyes. Rinse with water to remove.

Stop use if irritation occurs

and ask a doctor if a rash occurs.

Keep out of reach of children.

If swallowed, get medical help right away.

Directions

- Apply liberally and evenly 15 minutes before sun exposure.
- Children under 6 months of age: Ask a doctor.
- Sun Protection Measures. Spending time in the sun increases your risk of skin cancer and early skin aging. To decrease this risk, regularly use a sunscreen with a Broad Spectrum SPF value of 15 or higher and other sun protection measures including
- limit time in the sun, especially from 10 a.m. - 2 p.m.
- wear long-sleeved shirts, pants, hats, and sunglasses

Inactive Ingredients

Water/Aqua, Dimethicone, Talc, C12-15 Alkyl Benzoate, Isododecane, Cetyl PEG/PPG-10/1 Dimethicone, Isopentyldiol, Sorbitol, Tocopheryl Acetate, Phenoxyethanol, Sodium Chloride, Dimethicone/Vinyl Dimethicone Crosspolymer, Magnesium Sulfate, Sodium Dehydroacetate, Hydrogen Dimethicone, Potassium Sorbate, Disteardimonium Hectorite, Lecithin, Benzoic Acid, Aluminum Hydroxide, Alumina, Dehydroacetic Acid, Propylene Carbonate, Helianthus Annuus (Sunflower) Seed Oil, Triethoxycaprylylsilane, Tocopherol, Ethylhexylglycerin, Ascorbyl Palmitate, Citric Acid, Gardenia Florida Fruit Extract, Nelumbo Nucifera Flower Extract, Nymphaea Odorata Root Extract, Titanium Dioxide (CI 77891), Iron Oxides (CI 77491, CI 77492, CI 77499)

Other Information

Protect the product in this container from excessive heat and direct sun.

Questions?

Call 1-888-892-7273

Monday-Friday, 7am-4pm PST

Company Information

Dist. By Rare Beauty, LLC

El Segundo, CA 90245

Made in Italy

www.rarebeauty.com